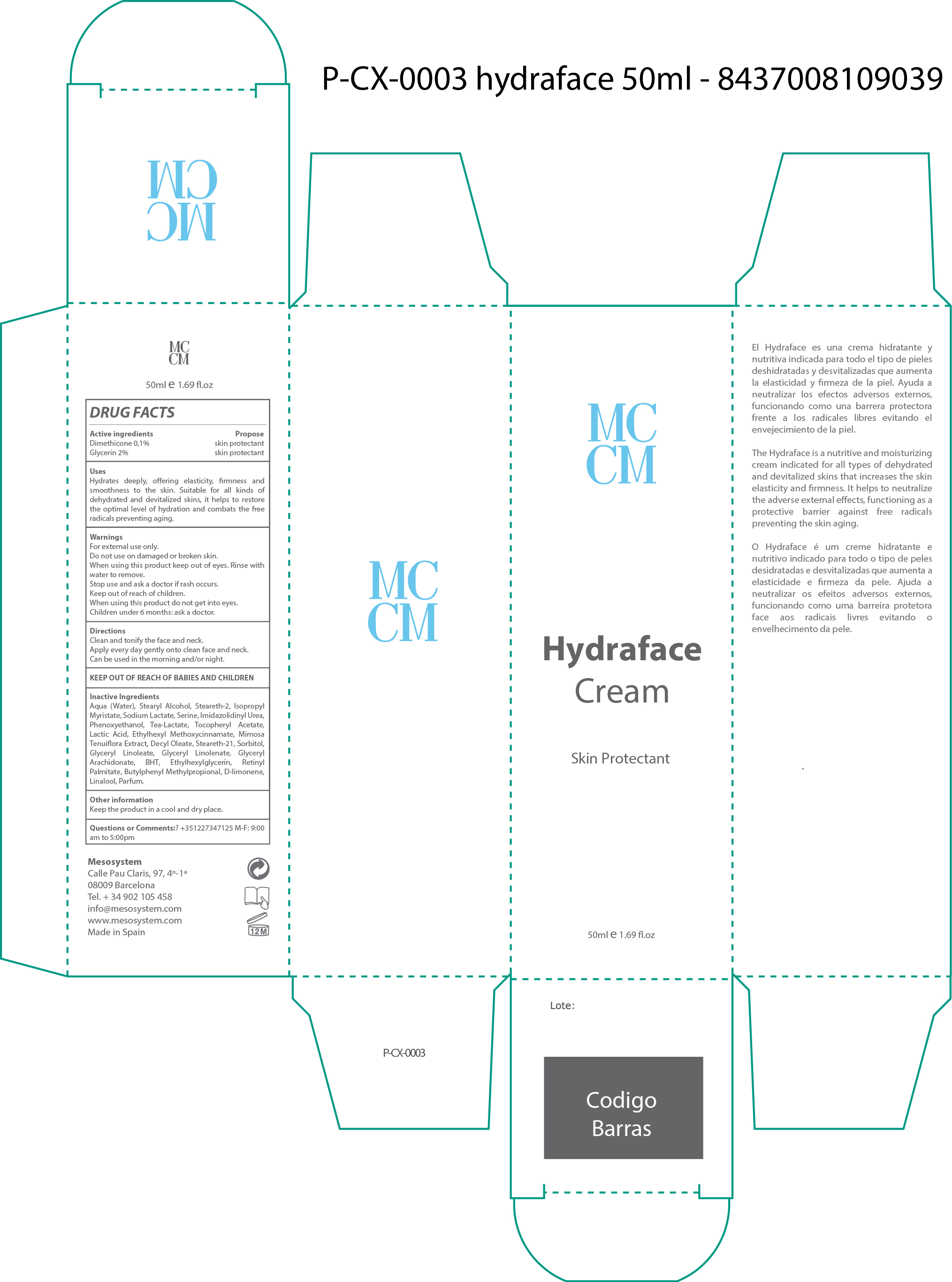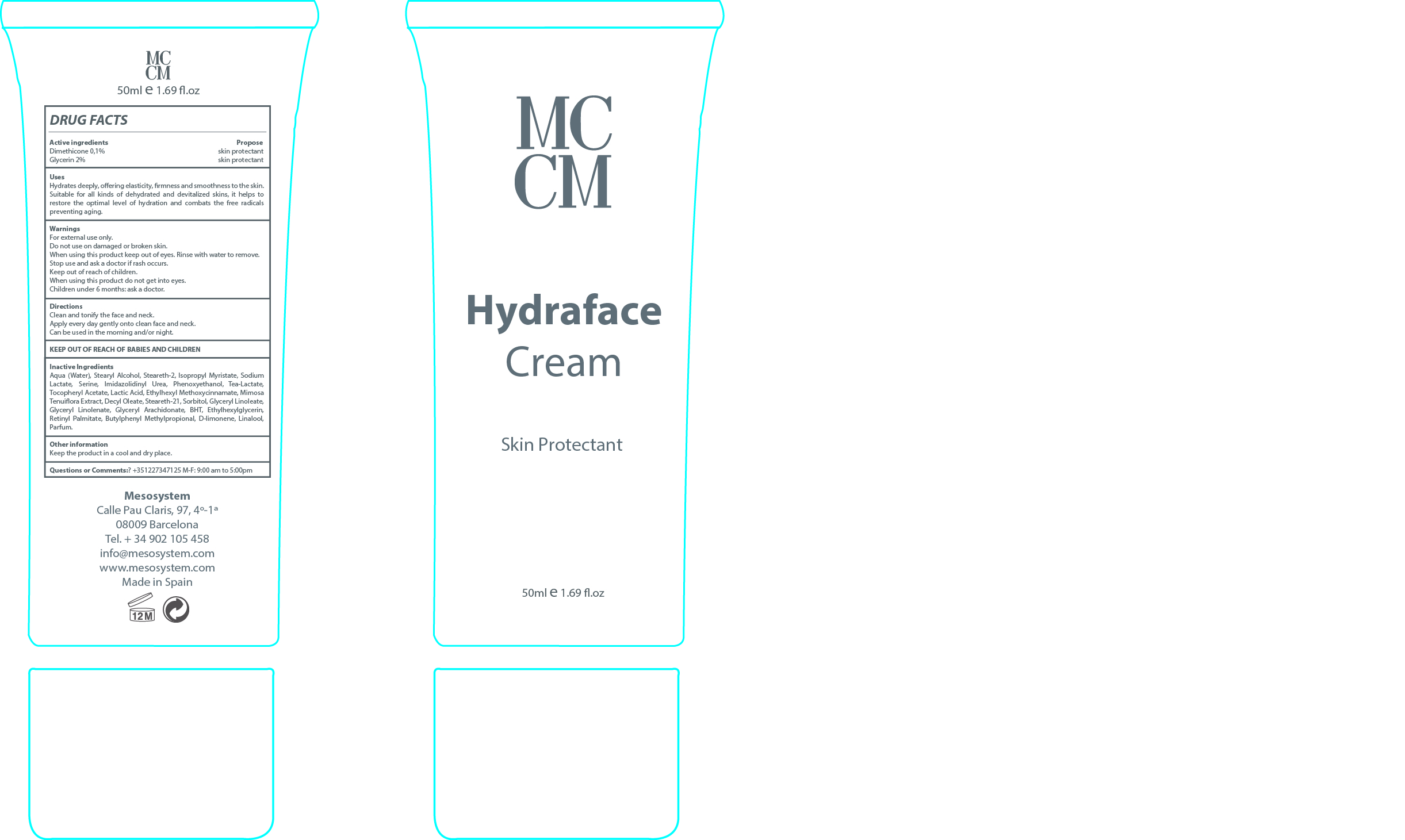 DRUG LABEL: Hydraface
NDC: 70663-009 | Form: CREAM
Manufacturer: MESO SYSTEM S A
Category: otc | Type: HUMAN OTC DRUG LABEL
Date: 20161217

ACTIVE INGREDIENTS: GLYCERIN 2 mg/1 mL; DIMETHICONE 0.1 mg/1 mL
INACTIVE INGREDIENTS: GLYCERYL LINOLENATE 0.1 mg/1 mL; PHENOXYETHANOL 0.9 mg/1 mL; DECYL OLEATE 0.1 mg/1 mL; STEARETH-21 0.1 mg/1 mL; SORBITOL 0.1 mg/1 mL; STEARETH-2 4 mg/1 mL; STEARYL ALCOHOL 4 mg/1 mL; WATER 76.65 mg/1 mL; ISOPROPYL MYRISTATE 4 mg/1 mL; SODIUM LACTATE 2 mg/1 mL; SERINE 2 mg/1 mL; IMIDUREA 2 mg/1 mL; TRIETHANOLAMINE LACTATE 0.5 mg/1 mL; ALPHA-TOCOPHEROL ACETATE 0.3 mg/1 mL; LACTIC ACID 0.1 mg/1 mL; ETHYLHEXYL METHOXYCRYLENE 0.1 mg/1 mL; MIMOSA TENUIFLORA LEAF 0.1 mg/1 mL; BUTYLATED HYDROXYTOLUENE 0.1 mg/1 mL; VITAMIN A PALMITATE 0.1 mg/1 mL; BUTYLPHENYL METHYLPROPIONAL 0.1 mg/1 mL; LIMONENE, (+)- 0.1 mg/1 mL; LINALOOL, (+)- 0.1 mg/1 mL; PEG-30 GLYCERYL LINOLEATE 0.1 mg/1 mL; GLYCERYL ARACHIDONATE 0.1 mg/1 mL; ETHYLHEXYLGLYCERIN 0.1 mg/1 mL; PERFLUNAFENE 0.05 mg/1 mL

HYDRAFACE CREAM

INACTIVE INGREDIENT

Water,Stearyl Alcohol, Steareth-2, Isopropyl Myristate, Sodium Lactate, Serine, Imidazolidinyl Urea. Phenoxyethanol.. Tea-Lactate

Tocopheryl Acetate.Lactic Acid. Ethylhexyl Methoxycinnamate.. Mimosa Tenuiflora Extract, Decyl Oleate, Steareth-21, Sorbitol, Glyceryl Linoleate, Glyceryl Linolenate,Glyceryl Arachidonate,BHT, Ethylhexylglycerin, Retinyl Palmitate, Butylphenyl Methylpropional, D-limonene, Linalool, Parfum

Warnings

- For external use only
- Do not use on damaged or broken sin

Stop use and ask a Doctor if

- Rash occurs
- When using this products keep out of eyes. Rinse with water to remove
- Children under 6 months: ask a doctor

WARNINGS

For external use only.

- When using this product do not get into eyes. Rinse with water to remove

Stop use and ask a Doctor if

- Rash occurs

USES

Hydrates deeple, offering elasticity, firmess and smoothness of the skin. Suitable for all kinds of dehyrated and devitalized skins. It helps to restore the optimun level of hydration and combats the free radicals prventing aging.

USES

Hydrates deeple, offering elasticity, firmess and smoothness of the skin. Suitable for all kinds of dehyrated and devitalized skins. It helps to restore the optimun level of hydration and combats the free radicals prventing aging.

Keep out of reach of babies and childrens

DIRECTIONS

- Clean and tonify te face and the neck
- Apply every day gently onto clean face and neck
- Can be used in the morning and/or night.

QUESTIONS OR COMMENTS?

+35 1227347125 M-F: 9:00 am to 5:00 pm

ACTIVE INGREDIENT

ACTIVE INGREDIENT PURPOSE

Dimethicone 0.1%..........................................Skin Protectant

Glycerin 2%....................................................Skin Protectant

PACKAGE LABEL

HYDRAFACE CREAM

Skin Protectant